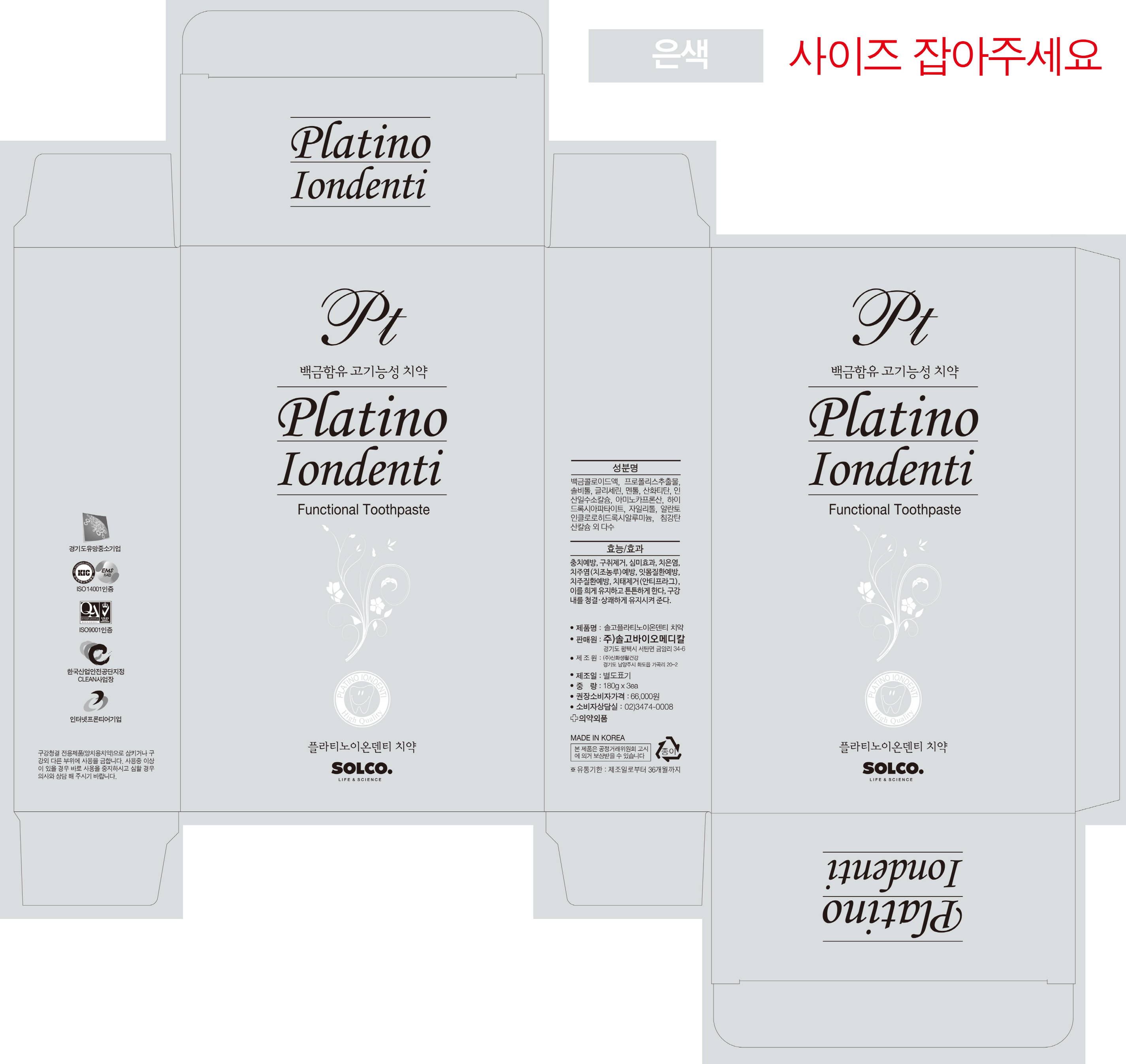 DRUG LABEL: Solco Platino Iondenti Tooth
NDC: 72370-0002 | Form: PASTE
Manufacturer: SOLCO BIOMEDICAL CO., LTD.
Category: otc | Type: HUMAN OTC DRUG LABEL
Date: 20180614

ACTIVE INGREDIENTS: AMINOCAPROIC ACID 0.02 g/100 g
INACTIVE INGREDIENTS: XYLITOL; ANHYDROUS DIBASIC CALCIUM PHOSPHATE

Drug Facts

ACTIVE INGREDIENT

Aminocaproic acid

INACTIVE INGREDIENT

Xylitol, Calcium Hydrogen Phosphate

PURPOSE

Toothpaste

keep out of reach of the children

INDICATIONS AND USAGE

Take a proper amount of toothpaste to the toothbrush and brush it

WARNINGS

If you have any problems, please consult your doctor.

DOSAGE AND ADMINISTRATION

for external use only